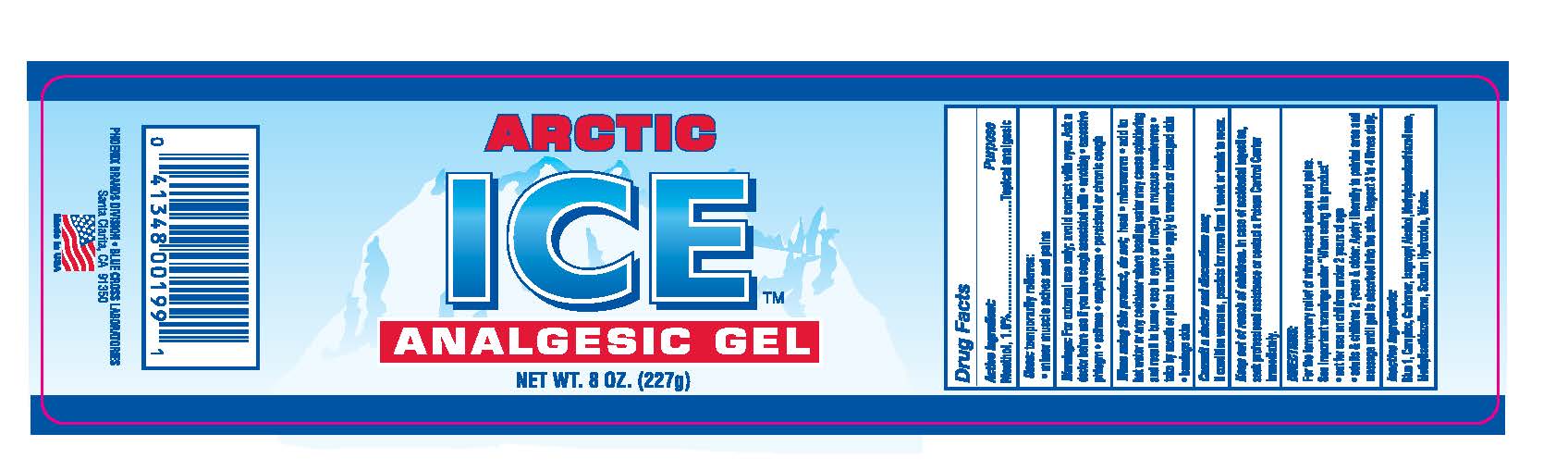 DRUG LABEL: Arctic Ice Analgesic
NDC: 22431-600 | Form: GEL
Manufacturer: Blue Cross Labs
Category: otc | Type: HUMAN OTC DRUG LABEL
Date: 20170127

ACTIVE INGREDIENTS: MENTHOL 1 g/100 g
INACTIVE INGREDIENTS: FD&C BLUE NO. 1; CAMPHOR (SYNTHETIC); CARBOMER 940; ISOPROPYL ALCOHOL; METHYLCHLOROISOTHIAZOLINONE; METHYLISOTHIAZOLINONE; SODIUM HYDROXIDE; WATER

Arctic Ice Analgesic Gel

Active Ingredient: Purpose

Menthol, 1% .................. Topical analgesic

PURPOSE

Uses: temporarily relieves:

- minor muscle aches and pains

Keep out of reach of children. In case of accidental ingestion, seek professional assistance or contact a Poison Control Center immediately

INDICATIONS AND USAGE

Consult a doctor and discontinue use;

if conditon worsens, persists for more than 1 week or tends to recur

WARNINGS

Warnings: For external use only; avoid contact with eyes. Ask a doctor before use if you have associated with

- smoking
- excessive phlegm
- asthma
- emphysema
- persisten or chronic cough

When using this product, do; heat

- microwave
- add to hot water or any container where healing water may cause splatter and result in burns
- use in eyes or directly on mucous membranes
- take by mouth or place in nostrils
- apply to wounds or damaged skin
- bandage skin

Directions:

For the temporary relief of minor muscle aches and pains. See important warnings under "When using this product"

- not for use on children under 2 years of age
- adults & children 2 year & older: Apply liberally to painful area and massage until gel is absorbed into the skin. Repeat 3 to 4 time daily.

INACTIVE INGREDIENT

Blue 1, Camphor, Carbomer, Isopropyl Alcohol, Methylchoroisothiazolinone, Methylisothiazolinone, Sodium Hydroxide, Water.

PACKAGE LABEL

Arctic Ice

Analgesic Gel

NET WT. 8 OZ. (227)